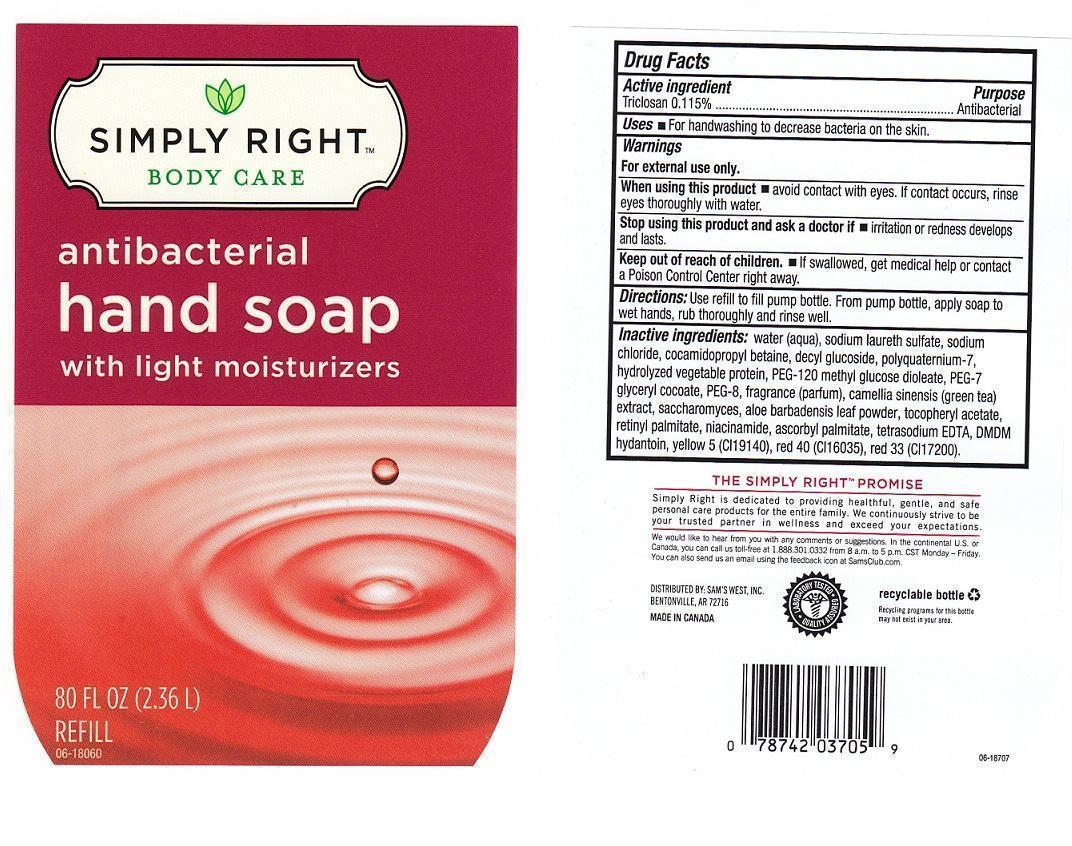 DRUG LABEL: SIMPLY RIGHT BODY CARE
NDC: 68196-146 | Form: LIQUID
Manufacturer: SAM'S WEST INC.
Category: otc | Type: HUMAN OTC DRUG LABEL
Date: 20130704

ACTIVE INGREDIENTS: TRICLOSAN 1.15 mg/1 mL
INACTIVE INGREDIENTS: WATER; SODIUM LAURETH SULFATE; SODIUM CHLORIDE; COCAMIDOPROPYL BETAINE; DECYL GLUCOSIDE; POLYQUATERNIUM-7 (70/30 ACRYLAMIDE/DADMAC; 1600000 MW); SOY PROTEIN; PEG-120 METHYL GLUCOSE DIOLEATE; PEG-7 GLYCERYL COCOATE; POLYETHYLENE GLYCOL 400; GREEN TEA LEAF; SACCHAROMYCES LYSATE; ALOE VERA LEAF; .ALPHA.-TOCOPHEROL ACETATE; VITAMIN A PALMITATE; NIACINAMIDE; ASCORBYL PALMITATE; EDETATE SODIUM; DMDM HYDANTOIN; FD&C YELLOW NO. 5; FD&C RED NO. 40; D&C RED NO. 33

DRUG FACTS

ACTIVE INGREDIENT

TRICLOSAN 0.115%

PURPOSE

ANTIBACTERIAL

USES

FOR HANDWASHING TO DECREASE BACTERIA ON THE SKIN.

WARNINGS

FOR EXTERNAL USE ONLY.

WHEN USING THIS PRODUCT

AVOID CONTACT WITH EYES. IF CONTACT OCCURS, RINSE EYES THOROUGHLY WITH WATER.

STOP USING THIS PRODUCT AND ASK A DOCTOR IF

IRRITATION OR REDNESS DEVELOPS AND LASTS.

KEEP OUT OF REACH OF CHILDREN

IF SWALLOWED, GET MEDICAL HELP OR CONTACT A POISON CONTROL CENTER RIGHT AWAY.

DIRECTIONS

USE REFILL TO FILL PUMP BOTTLE. FROM PUMP BOTTLE, APPLY SOAP TO WET HANDS, RUB THOROUGHLY AND RINSE WELL.

INACTIVE INGREDIENTS:

WATER (AQUA), SODIUM LAURETH SULFATE, SODIUM CHLORIDE, COCAMIDOPROPYL BETAINE, DECYL GLUCOSIDE, POLYQUATERNIUM-7, HYDROLYZED VEGETABLE PROTEIN, PEG-120 METHYL GLUCOSE DIOLEATE, PEG-7 GLYCERYL COCOATE, PEG-8, FRAGRANCE (PARFUM), CAMELLIA SINENSIS (GREEN TEA) EXTRACT, SACCHAROMYCES, ALOE BARBADENSIS LEAF POWDER, TOCOPHERYL ACETATE, RETINYL PALMITATE, NIACINAMIDE, ASCORBYL PALMITATE, TETRASODIUM EDTA, DMDM HYDANTOIN, YELLOW 5 (CI 19140), RED 40 (CI 16035), RED 33 (CI 17200).